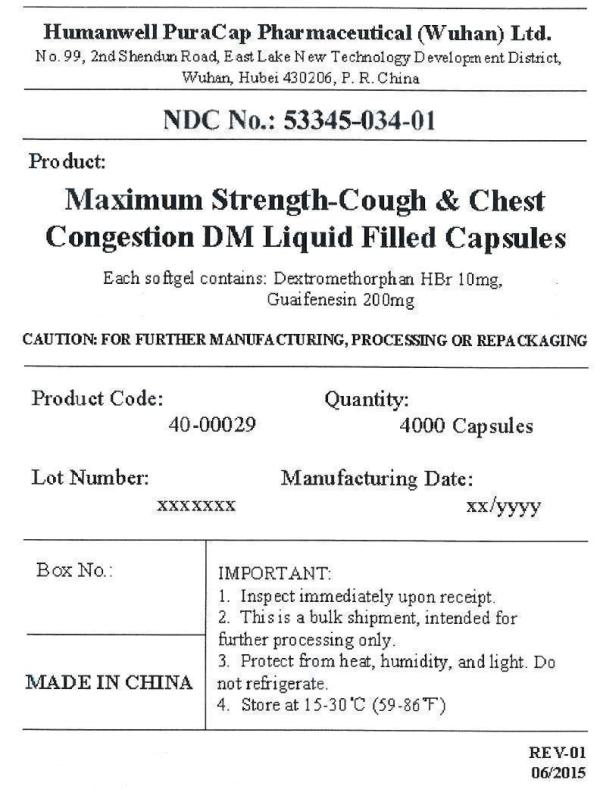 DRUG LABEL: Maximum Strength-Cough and Chest Congestion DM
NDC: 53345-034 | Form: CAPSULE, LIQUID FILLED
Manufacturer: Humanwell PuraCap Pharmaceutical (Wuhan) Co., Ltd.
Category: otc | Type: HUMAN OTC DRUG LABEL
Date: 20241125

ACTIVE INGREDIENTS: DEXTROMETHORPHAN HYDROBROMIDE 10 mg/1 1; GUAIFENESIN 200 mg/1 1
INACTIVE INGREDIENTS: FD&C RED NO. 40; GELATIN; GLYCERIN; POLYETHYLENE GLYCOL, UNSPECIFIED; POVIDONE; PROPYLENE GLYCOL; SORBITOL; WATER

Maximum Strength-Cough and Chest Congestion DM Liquid Filled Capsules

Drug Facts

Active ingredient (in each softgel)

Dextromethorphan HBr, USP 10 mg

Guaifenesin, USP 200 mg

Purpose

Cough suppressant

Expectorant

Uses

- temporarily relieves cough due to minor throat and bronchial irritation as may occur with a cold
- helps loosen phlegm (mucus) and thin bronchial secretions to drain bronchial tubes

Warnings

Do not use if

you are now taking a prescription monoamine oxidase inhibitor (MAOI) (certain drugs for depression, psychiatric, or emotional conditions, or Parkinson's disease), or for 2 weeks after stopping the MAOI drug. If you do not know if your prescription drug contains an MAOI, ask a doctor or pharmacist before taking this product.

Ask a doctor before use if you have
• cough that occurs with too much phlegm (mucus)
• cough that lasts or is chronic such as occurs with smoking, asthma, chronic bronchitis, or emphysema

Stop use and ask a doctor if

cough lasts for more than 7 days, comes back, or is accompanied by fever, rash, or persistent headache. These could be signs of a serious condition.

PREGNANCY OR BREAST FEEDING

If pregnant or breast-feeding,ask a health professional before use.

Keep out of reach of children.In case of overdose, get medical help or contact a Poison Control Center right away.

Directions

• do not take more than 12 softgels in any 24-hour period
• this adult product is not intended for use in children under 12 years of age

age | dose
adults and children 12 years and over | 2 softgels every 4 hours
children under 12 years | do not use

Other information

• store at room temperature 15-30°C (59-86°F)
• avoid excessive heat above 40°C (104°F)

Inactive ingredients

FD&C Red #40, gelatin, glycerin, polyethylene glycol, povidone, propylene glycol, purified water, sorbitol special and white edible ink

Manufactured by:
Humanwell PuraCap Pharmaceutical (Wuhan) Co., Ltd.
Wuhan, Hubei
430206, China

PRINCIPAL DISPLAY PANEL - Shipping Label

Maximum Strength-Cough and Chest Congestion DM Liquid Filled Capsules
Quantity : 4000 Capsules
NDC. No : 53345-034-01

IMPORTANT:

Inspect immediately upon receipt.
This is a bulk shipment, intended for further processing only.
Protect from heat, humidity, and light. Do not refrigerate.
Store at 15-30°C (59-86°F)

CAUTION : FOR FURTHER MANUFACTURING, PROCESSING OR REPACKAGING